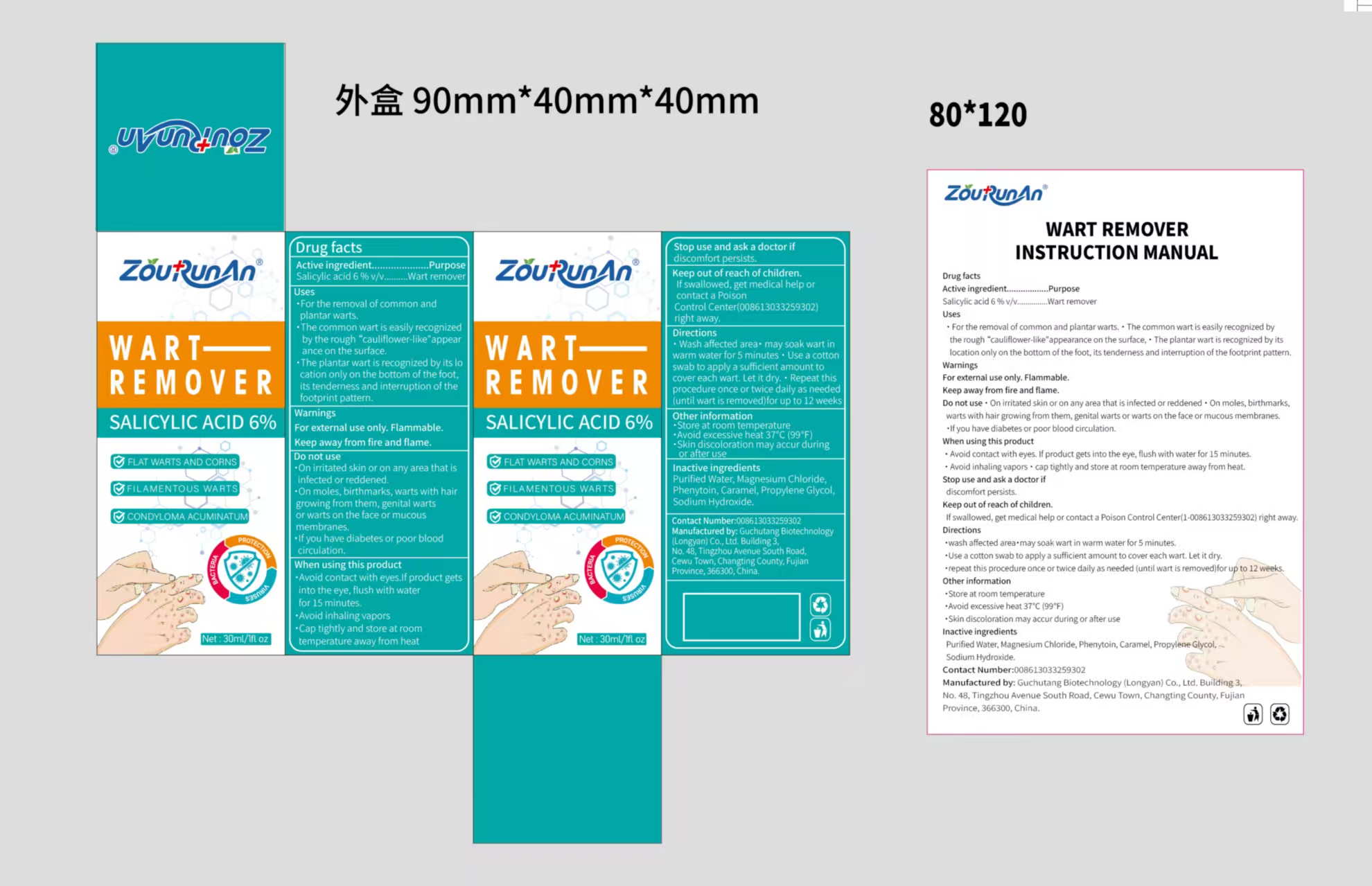 DRUG LABEL: zourunan WART REMOVER
NDC: 87083-005 | Form: LIQUID
Manufacturer: Guchutang Biotechnology (Longyan) Co., Ltd
Category: otc | Type: HUMAN OTC DRUG LABEL
Date: 20251106

ACTIVE INGREDIENTS: SALICYLIC ACID 6 g/100 mL
INACTIVE INGREDIENTS: SODIUM HYDROXIDE; CARAMEL; PHENYTOIN; MAGNESIUM CHLORIDE; PROPYLENE GLYCOL; WATER

87083-005

Active Ingredient

Salicylic acid 6 % v/v

Purpose

wart remover

Use

·For the removal of common and plantar warts
·The common wart is easily recognized by the rough “cauliflower-like"appearance on the surface,
·The plantar wart is recognized by its location only on the bottom of the foot, its tenderness and interruption of the footprint pattern.

Warnings

For external use only. Flammable.
Keep away from fire and flame.

Do not use

·On irritated skin or on any area that is infected or reddened
·On moles, birthmarks, warts with hair growing from them, genital warts or warts on the face or mucous membranes.
·If you have diabetes or poor blood circulation.

When Using

·Avoid contact with eyes.If product gets into the eye, flush with water for 15 minutes.
·Avoid inhaling vapors

·Cap tightly and store at room temperature away from heat.

Stop Use

if discomfort persists

Ask Doctor

if discomfort persists

Keep Out Of Reach Of Children

If swallowed, get medical help or contact a Poison Control Center right away.

Directions

·Wash affected area·may soak wart in warm water for 5 minutes.
·Use a cotton swab to apply a sufficient amount to cover each wart. Let it dry.
·Repeat this procedure once or twice daily as needed (until wart is removed)for up to 12 weeks.

Other information

·Store at room temperature
·Avoid excessive heat 37℃ (99℉)
·Skin discoloration may accur during or after use

Inactive ingredients

Purified Water, Magnesium Chloride, Phenytoin, Caramel, Propylene Glycol, Sodium Hydroxide